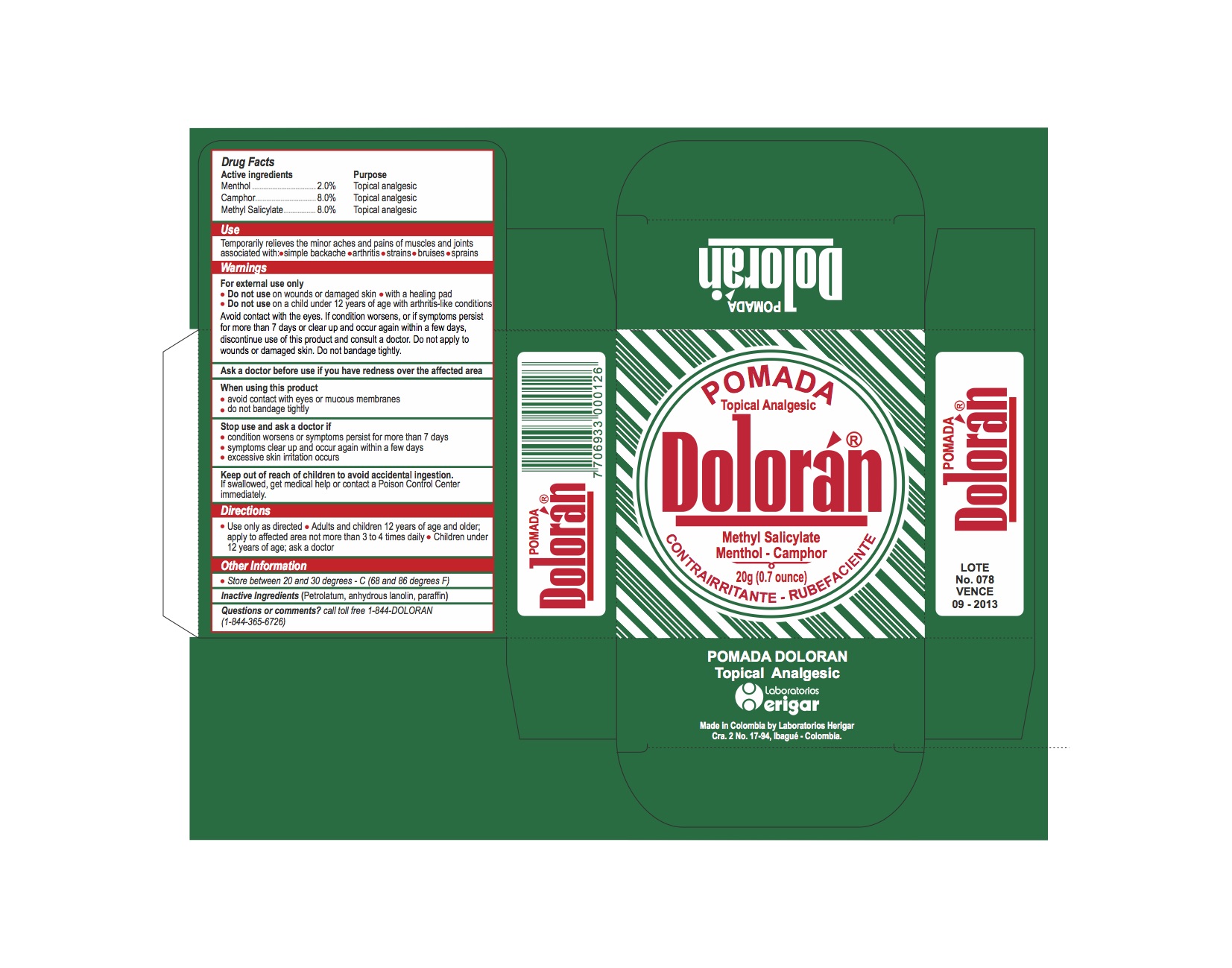 DRUG LABEL: Doloran
NDC: 71016-001 | Form: OINTMENT
Manufacturer: Hector Rivera Garzon y Compania. S. en C.
Category: otc | Type: HUMAN OTC DRUG LABEL
Date: 20191227

ACTIVE INGREDIENTS: MENTHOL 0.08 g/1 g; CAMPHOR, (-)- 0.08 g/1 g; METHYL SALICYLATE 0.02 g/1 g
INACTIVE INGREDIENTS: LANOLIN; PARAFFIN; PETROLATUM

Active Ingredients

Active Ingredients Purpose

Menthol _______________________________ 2.0% Topical Analgesic

Camphor ______________________________ 8.0% Topical Analgesic

Methyl Salicylate_________________________ 8.0% Topical Analgesic

Purpose

Topical Analgesic

Use

Temporarily relieves the minor aches and pains of muscles and joints associated with:

- simple backache
- arthritis
- strains
- bruises
- sprains

Warnings

For external use only

- Do not use on wounds or damaged skin with a healing pad
- Do not use on a child under 12 years of age with arthritis-like conditions

Avoid contact with the eyes. If condition worsens, or if symptoms persist for more than 7 days or clear up and occur again within a few days, discontinue use of htis product and consult a doctor. Do not apply to wounds or damaged skin. Do not bandage tightly

Keep out of reach of children to avoid accidental ingestion.

If swallowed, get medical help or contact a Poison Control Center immediately.

Directions

- Use only as directed
- Adults and children 12 years of age and older; apply to affected area not ore than 3 to 4 times daily
- Children under 12 years of age; ask a doctor

Inactive Ingredients (Petrolatum, anhydrous lanolin, parrafin)